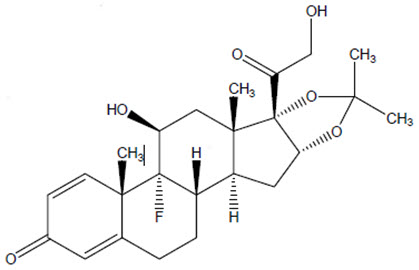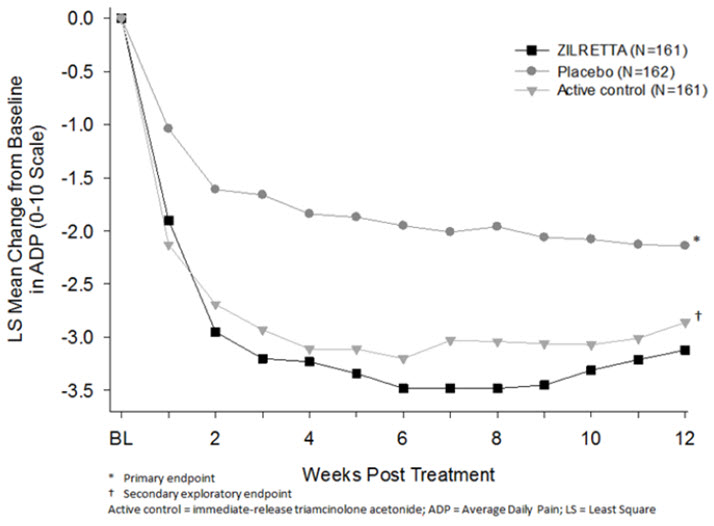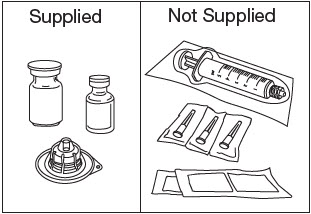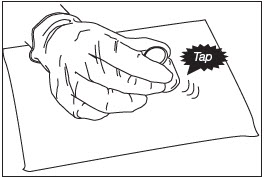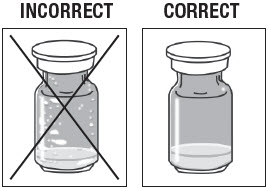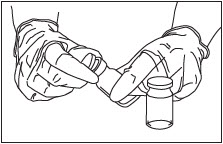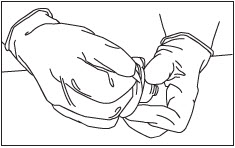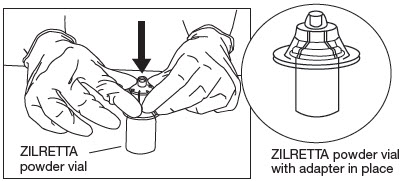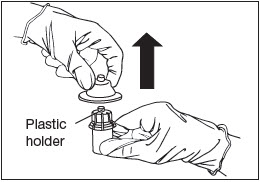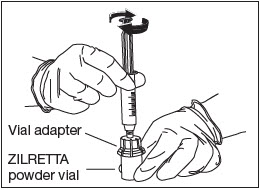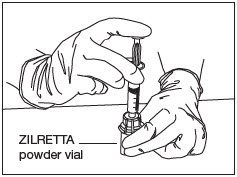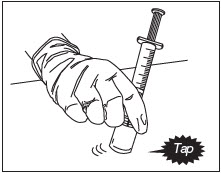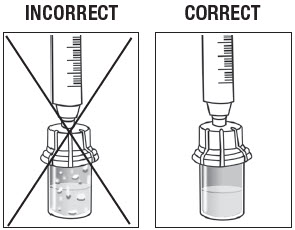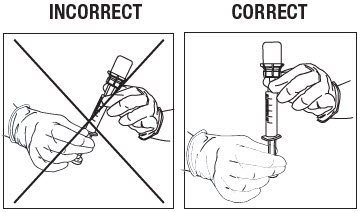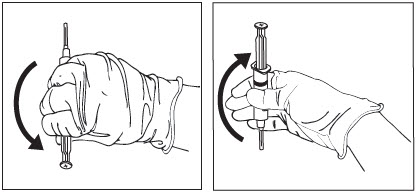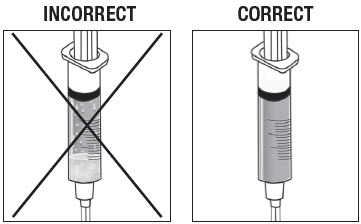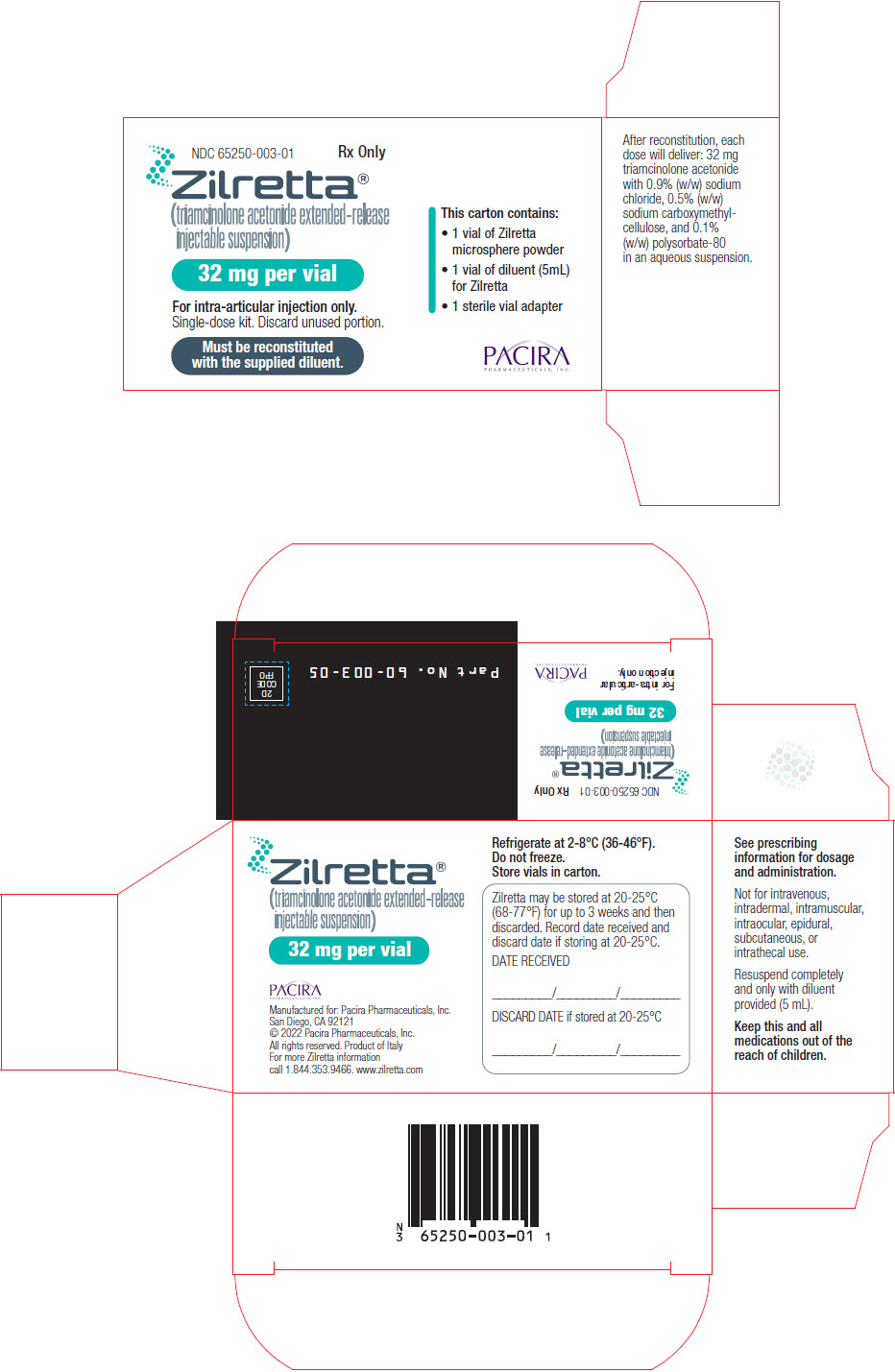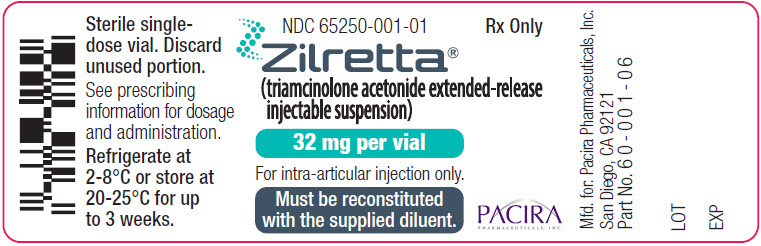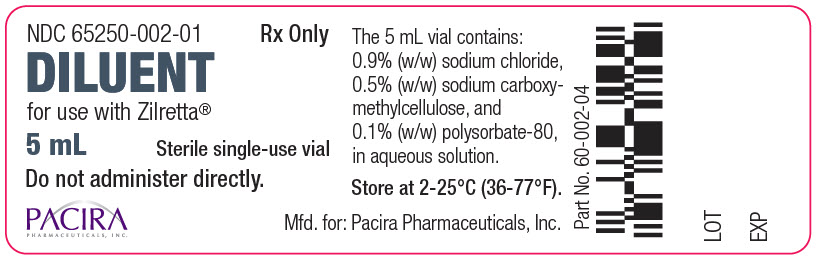 DRUG LABEL: Zilretta
NDC: 65250-003 | Form: KIT | Route: INTRA-ARTICULAR
Manufacturer: Pacira Pharmaceuticals, Inc.
Category: prescription | Type: HUMAN PRESCRIPTION DRUG LABEL
Date: 20250605

ACTIVE INGREDIENTS: TRIAMCINOLONE ACETONIDE 32 mg/1 1

HIGHLIGHTS OF PRESCRIBING INFORMATION

These highlights do not include all the information needed to use ZILRETTA safely and effectively. See full prescribing information for ZILRETTA.
ZILRETTA® (triamcinolone acetonide extended-release injectable suspension), for intra-articular use
Initial U.S. Approval: 1957

1 INDICATIONS AND USAGE

ZILRETTA is an extended-release synthetic corticosteroid indicated as an intra-articular injection for the management of osteoarthritis pain of the knee. (1)

Limitation of Use

The efficacy and safety of repeat administration of ZILRETTA have not been demonstrated. (2.1)

2 DOSAGE AND ADMINISTRATION

- 32 mg (5 mL) administered as a single intra-articular injection in the knee. (2.1)
- See Instructions for Use (IFU) for instructions on reconstitution of ZILRETTA with the supplied diluent. (2.2)
- It is normal for some residue to be left behind on the vial walls after withdrawing the suspension. (2.2)
- ZILRETTA is NOT substitutable with other formulations of injectable triamcinolone acetonide. (2.3)

3 DOSAGE FORMS AND STRENGTHS

ZILRETTA is an injectable suspension that delivers 32 mg of triamcinolone acetonide. It is supplied as a single-dose kit containing one vial of ZILRETTA microsphere powder, one vial of 5 mL diluent, and one sterile vial adapter. (3)

4 CONTRAINDICATIONS

Patients with hypersensitivity to triamcinolone acetonide or any component of the product. (4)

5 WARNINGS AND PRECAUTIONS

- Intra-articular Use Only: Do not administer ZILRETTA by epidural, intrathecal, intravenous, intraocular, intramuscular, intradermal, or subcutaneous routes. (5.1)
- Serious Neurologic Adverse Reactions with Epidural and Intrathecal Administration: Serious neurologic events have been reported following epidural or intrathecal corticosteroid administration. Corticosteroids are not approved for this use. (5.2)
- Hypersensitivity Reactions: Serious reactions have been reported with triamcinolone acetonide injection. Institute appropriate care upon occurrence of an anaphylactic reaction. (5.3)
- Joint Infection and Damage: May cause joint pain accompanied by joint swelling. If this occurs, conduct appropriate evaluation to exclude septic arthritis and institute appropriate antimicrobial therapy if septic arthritis is confirmed. (5.4)

6 ADVERSE REACTIONS

Most commonly reported adverse reactions (incidence ≥1%) in clinical studies include sinusitis, cough, and contusions. (6)

To report SUSPECTED ADVERSE REACTIONS, contact Pacira Pharmaceuticals, Inc. at 1-844-353-9466 or FDA at 1-800-FDA-1088 or www.fda.gov/medwatch.

FULL PRESCRIBING INFORMATION

1 INDICATIONS AND USAGE

ZILRETTA (triamcinolone acetonide extended-release injectable suspension) is indicated as an intra-articular injection for the management of osteoarthritis pain of the knee.

Limitation of Use

The efficacy and safety of repeat administration of ZILRETTA have not been demonstrated. [see Dosage and Administration (2.1)].

2 DOSAGE AND ADMINISTRATION

2.1 Important Dosage and Administration Information

- ZILRETTA is administered as a single intra-articular extended-release injection of triamcinolone acetonide, to deliver 32 mg (5 mL).
- ZILRETTA is for intra-articular use only. Do NOT administer by the following routes: epidural, intrathecal, intravenous, intraocular, intramuscular, intradermal, subcutaneous.
- ZILRETTA is not suitable for use in small joints, such as the hand.
- The efficacy and safety of repeat administration of ZILRETTA have not been demonstrated [see Adverse Reactions (6) and Nonclinical Toxicology (13.2)].
- The efficacy and safety of ZILRETTA for management of osteoarthritis pain of shoulder and hip have not been evaluated.

2.2 Preparation and Administration of Intra-Articular Suspension

Refer to the Instructions for Use for directions on the preparation and administration of ZILRETTA.

ZILRETTA is supplied as a single-dose kit containing a vial of ZILRETTA microsphere powder, a vial of sterile diluent, and a sterile vial adapter.

ZILRETTA must be prepared using the diluent supplied in the kit.

Preparation of ZILRETTA requires close attention to the Instructions for Use to ensure successful administration.

Use proper aseptic technique throughout the dose preparation and administration procedure.

ZILRETTA is a suspension product and it is normal for some residue to be left behind on the vial walls after withdrawing the contents.

Promptly inject ZILRETTA after preparation to avoid settling of the suspension. If needed, the ZILRETTA suspension can be stored in the vial for up to 4 hours at ambient conditions. Gently swirl the vial to resuspend any of the settled microspheres prior to preparing the syringe for injection.

The usual technique for intra-articular injection should be followed. Aspiration of synovial fluid may be performed based on clinical judgment prior to administration of ZILRETTA.

2.3 Non-Interchangeability with Other Formulations of Triamcinolone Acetonide for Intra-articular Use

ZILRETTA is NOT substitutable with other formulations of injectable triamcinolone acetonide.

3 DOSAGE FORMS AND STRENGTHS

ZILRETTA is an injectable suspension that delivers 32 mg of triamcinolone acetonide. ZILRETTA is supplied as a single-dose kit, containing:

- One vial of ZILRETTA white to off-white microsphere powder
- One vial of 5 mL sterile, colorless to pale yellow, clear diluent
- One sterile vial adapter

4 CONTRAINDICATIONS

ZILRETTA is contraindicated in patients who are hypersensitive to triamcinolone acetonide, corticosteroids or any components of the product [see Warnings and Precautions (5.3) and How Supplied/Storage and Handling (16)].

5 WARNINGS AND PRECAUTIONS

5.1 Warnings and Precautions Specific for ZILRETTA

ZILRETTA has not been evaluated and should not be administered by the following routes:

- Epidural
- Intrathecal
- Intravenous
- Intraocular
- Intramuscular
- Intradermal
- Subcutaneous

[see Warnings and Precautions (5.2)].

5.2 Serious Neurologic Adverse Reactions with Epidural and Intrathecal Administration

Serious neurologic events, some resulting in death, have been reported with epidural injection of corticosteroids. Specific events reported include, but are not limited to, spinal cord infarction, paraplegia, quadriplegia, cortical blindness, and stroke [see Adverse Reactions (6)]. These serious neurologic events have been reported with and without use of fluoroscopy.

Reports of serious medical events have been associated with the intrathecal route of corticosteroid administration [see Adverse Reactions (6)].

The safety and effectiveness of epidural and intrathecal administration of corticosteroids have not been established, and corticosteroids are not approved for this use. In particular, the formulation of ZILRETTA should not be considered safe to use for epidural or intrathecal administration.

5.3 Hypersensitivity Reactions

Rare instances of anaphylaxis have occurred in patients with hypersensitivity to corticosteroids. Cases of serious anaphylaxis, including death, have been reported in individuals receiving triamcinolone acetonide injection, regardless of the route of administration [see Adverse Reactions (6)]. Institute appropriate care upon occurrence of an anaphylactic reaction.

5.4 Joint Infection and Damage

Intra-articular injection of corticosteroid may be complicated by joint infection. A marked increase in pain accompanied by local swelling, further restriction of joint motion, fever, and malaise are suggestive of septic arthritis. If this complication occurs and a diagnosis of septic arthritis is confirmed, institute appropriate antimicrobial therapy [see Adverse Reactions (6)].

Avoid injection of a corticosteroid into an infected site. Local injection of a corticosteroid into a previously infected joint is not usually recommended. Examine any joint fluid present to exclude a septic process.

Corticosteroid injection into unstable joints is generally not recommended.

Intra-articular injection may result in damage to joint tissues.

5.5 Increased Risk of Infections

Intra-articularly injected corticosteroids are systemically absorbed. Patients who are on corticosteroids are more susceptible to infections than are healthy individuals. There may be decreased resistance and inability to localize infection when corticosteroids are used. Infection with any pathogen (viral, bacterial, fungal, protozoan, or helminthic) in any location of the body may be associated with the use of corticosteroids alone or in combination with other immunosuppressive agents. These infections may be mild to severe. With increasing doses of corticosteroids, the rate of occurrence of infectious complications increases. Corticosteroids may also mask some signs of current infection.

Advise patients to inform their health care provider if they develop fever or other signs or symptoms of infection. Advise patients who have not been vaccinated to avoid exposure to chicken pox or measles. Instruct patients to contact their health care provider immediately if they are exposed [see Patient Counseling Information (17)].

5.6 Alterations in Endocrine Function

Corticosteroids can produce reversible hypothalamic-pituitary-adrenal axis suppression, with the potential for adrenal insufficiency after withdrawal of treatment, which may persist for months.

In situations of stress during that period (as in trauma, surgery, or illness), institute corticosteroid replacement therapy.

Metabolic clearance of corticosteroids is decreased in hypothyroid patients and increased in hyperthyroid patients.

5.7 Cardiovascular Effects

Corticosteroids can cause elevations of blood pressure, salt and water retention, and increased excretion of potassium. These effects are less likely to occur with synthetic derivatives.

Monitor patients with congestive heart failure or hypertension for signs of edema, weight gain, and imbalance in serum electrolytes. Dietary salt restriction and potassium supplementation may be necessary.

5.8 Renal Effects

Corticosteroids can cause salt and water retention, and increased excretion of potassium. These effects are less likely to occur with synthetic derivatives. All corticosteroids increase calcium excretion.

Monitor patients with renal insufficiency for signs of edema, weight gain, and imbalance in serum electrolytes. Dietary salt restriction and potassium supplementation may be necessary.

5.9 Increased Intraocular Pressure

Corticosteroid use may be associated with development or exacerbation of increased intraocular pressure.

Monitor patients with elevated intraocular pressure for potential treatment adjustment.

5.10 Gastrointestinal Perforation

Corticosteroid administration is associated with increased risk of gastrointestinal perforation in patients with certain GI disorders such as active or latent peptic ulcers, diverticulosis, diverticulitis, ulcerative colitis and in patients with fresh intestinal anastomoses.

Avoid corticosteroids in these patients because signs of peritoneal irritation following gastrointestinal perforation may be minimal or absent.

5.11 Alterations in Bone Density

Corticosteroids decrease bone formation and increase bone resorption through their effect on calcium regulation and inhibition of osteoblast function.

Special consideration should be given to patients with or at increased risk of osteoporosis (e.g., postmenopausal women) before initiating corticosteroid therapy.

5.12 Behavioral and Mood Disturbances

Corticosteroid use may be associated with new or aggravated adverse psychiatric reactions ranging from euphoria, insomnia, mood swings, and personality changes to severe depression and frank psychotic manifestations.

Special consideration should be given to patients with previous or current emotional instability or psychiatric illness before initiating corticosteroid therapy. Advise patients and/or caregivers to immediately report any new or worsening behavior or mood disturbances to their health care provider.

6 ADVERSE REACTIONS

The following serious adverse reactions are described elsewhere in the labeling.

- Serious Neurologic Adverse Reactions with Epidural and Intrathecal Administration [see Warnings and Precautions (5.2)]
- Hypersensitivity Reactions [see Warnings and Precautions (5.3)]
- Joint Infection and Damage [see Warnings and Precautions (5.4)]
- Increased Risk of Infections [see Warnings and Precautions (5.5)]
- Alterations in Endocrine Function [see Warnings and Precautions (5.6)]
- Cardiovascular Effects [see Warnings and Precautions (5.7)]
- Renal Effects [see Warnings and Precautions (5.8)]
- Increased Intraocular Pressure [see Warnings and Precautions (5.9)]
- Gastrointestinal Perforation [see Warnings and Precautions (5.10)]
- Alternations in Bone Density [see Warnings and Precautions (5.11)]
- Behavioral and Mood Disturbances [see Warnings and Precautions (5.12)]

6.1 Clinical Trials

Because clinical studies are conducted under widely varying conditions, adverse reaction rates observed in the clinical trials of a drug cannot be directly compared to rates in the clinical trials of another drug and may not reflect the rates observed in practice.

The data below reflect exposure to a single 32 mg intra-articular injection of ZILRETTA in clinical studies in patients with moderate to severe pain due to osteoarthritis of the knee. Clinical studies included randomized, double-blind, parallel-group, placebo and/or active-controlled, and pharmacokinetic/pharmacodynamic studies with follow-up ranging from 6-24 weeks. A total of 424 patients received ZILRETTA and 262 received placebo. Treatment emergent adverse reactions reported by greater than or equal to 1% of patients in the ZILRETTA arms are summarized below (Table 1 and 2).

Overall, the incidence and nature of adverse reactions was similar to that observed with placebo.

Table 1: Most Commonly Reported Treatment-Emergent Adverse Reactions with ZILRETTA (Incidence ≥1%) in Patients with Osteoarthritis of the Knee
Preferred Term (MedDRA) | ZILRETTA (N=424) | Placebo (N=262)
Sinusitis | 2% | 1%
Cough | 2% | 1%
Contusions | 2% | 1%

Table 2: Most Commonly Reported Treatment-Emergent Injected Knee Adverse Reactions with ZILRETTA (Incidence ≥1%) in Patients with Osteoarthritis of the Knee
Preferred Term (MedDRA) | ZILRETTA (N=424) | Placebo (N=262)
Joint Swelling | 3% | 2%
Contusions | 2% | 1%

The safety of repeat administration of ZILRETTA was evaluated in a multicenter, open-label, single-arm study in patients with osteoarthritis pain of the knee. A total of 179 patients received a repeat injection on or after Week 12 (median 16.6 weeks) and were followed for 52 weeks from the initial injection. As assessed by adverse event rates for the periods of baseline to second dose and second dose to the comparable period after the second dose, there were higher rates of reported mild to moderate arthralgia after the second dose (16%) than after the first dose (6%). The data from this study are insufficient to fully characterize the safety of repeat administration of ZILRETTA. [See also Nonclinical Toxicology (13.2)].

6.2 Post-marketing Experience

The following adverse reactions, presented alphabetically by body system, have been identified during post-approval use of ZILRETTA. Because these reactions are reported voluntarily from a population of uncertain size, it is not always possible to reliably estimate their frequency or establish a causal relationship to drug exposure.

Endocrine: Increased blood glucose (in diabetic patients).

General and administration site conditions: Pain including injection site pain or discomfort and leg pain.

Immune system: Hypersensitivity reactions including pruritus, rash, angioedema, and anaphylaxis [see Contraindications (4), Warnings and Precautions (5.3)].

Infections and Infestations: Septic arthritis [see Warning and Precautions (5.4)].

Musculoskeletal: Arthralgia, joint swelling or effusion, muscle spasms.

Nervous system: Headache.

Reproductive system: Postmenopausal vaginal bleeding (similar to a menstrual period).

Skin and Subcutaneous Tissue: Pruritus.

6.3 Corticosteroid Adverse Reactions

The following adverse reactions, presented alphabetically by body system, are from voluntary reports or clinical studies of corticosteroids. Because some of these reactions are reported voluntarily from a population of uncertain size, it is not always possible to reliably estimate their frequency or establish a causal relationship to drug exposure.

Anaphylactic reactions: Anaphylaxis including death, angioedema [see Warnings and Precautions (5.3)].

Cardiovascular: Bradycardia, cardiac arrest, cardiac arrhythmias, cardiac enlargement, circulatory collapse, congestive heart failure, hypertension [see Warnings and Precautions (5.7)], fat embolism, hypertrophic cardiomyopathy in premature infants, myocardial rupture following recent myocardial infarction, pulmonary edema, syncope, tachycardia, thromboembolism, thrombophlebitis, vasculitis.

Dermatologic: Acne, allergic dermatitis, cutaneous and subcutaneous atrophy, dry scaly skin, ecchymoses and petechiae, edema, erythema, hyperpigmentation, hypopigmentation, impaired wound healing, increased sweating, lupus erythematosus-like lesions, purpura, rash, sterile abscess, striae, suppressed reactions to skin tests, thin fragile skin, thinning scalp hair, urticaria.

Endocrine: Decreased carbohydrate and glucose tolerance, development of Cushingoid state, glycosuria, hirsutism, hypertrichosis, increased requirements for insulin or oral hypoglycemic agents in diabetes, manifestations of latent diabetes mellitus, menstrual irregularities, secondary adrenocortical and pituitary unresponsiveness (particularly in times of stress, as in trauma, surgery, or illness), suppression of growth in pediatric patients.

Fluid and electrolyte disturbances: Congestive heart failure in susceptible patients [see Warnings and Precautions (5.7)], fluid retention, sodium retention.

Gastrointestinal: Abdominal distention, bowel/bladder dysfunction (after intrathecal administration) [see Warnings and Precautions (5.2)], elevation in serum liver enzyme levels (usually reversible upon discontinuation), hepatomegaly, increased appetite, nausea, pancreatitis, peptic ulcer with possible perforation and hemorrhage, perforation of the small and large intestine (particularly in patients with inflammatory bowel disease) [see Warnings and Precautions (5.10)], ulcerative esophagitis.

Metabolic: Negative nitrogen balance due to protein catabolism.

Musculoskeletal: Aseptic necrosis of femoral and humeral heads, calcinosis (following intra-articular or intralesional use), Charcot-like arthropathy, loss of muscle mass, muscle weakness, osteoporosis, pathologic fracture of long bones, post injection flare (following intra-articular use), steroid myopathy, tendon rupture, vertebral compression fractures.

Neurologic/Psychiatric: Convulsions, depression, emotional instability, euphoria, headache, increased intracranial pressure with papilledema (pseudotumor cerebri) usually following discontinuation of treatment, insomnia, mood swings, neuritis, neuropathy, paresthesia, personality changes, psychiatric disorders [see Warnings and Precautions (5.12)], vertigo. Arachnoiditis, meningitis, paraparesis/paraplegia, and sensory disturbances have occurred after intrathecal administration. Spinal cord infarction, paraplegia, quadriplegia, cortical blindness, and stroke (including brainstem) have been reported after epidural administration of corticosteroids [see Warnings and Precautions (5.2)].

Ophthalmic: Exophthalmos, glaucoma, increased intraocular pressure [see Warnings and Precautions (5.9)], posterior subcapsular cataracts, rare instances of blindness associated with periocular injections.

Other: Abnormal fat deposits, decreased resistance to infection, hiccups, increased or decreased motility and number of spermatozoa, malaise, moon face, weight gain.

7 DRUG INTERACTIONS

No drug-drug interaction studies have been conducted with ZILRETTA. Table 3 contains drug interactions associated with systemic corticosteroids.

Table 3: Drug Interactions Associated with Systemic Corticosteroids
Aminoglutethimide | Aminoglutethimide may lead to a loss of corticosteroid-induced adrenal suppression.
Amphotericin B injection and potassium-depleting agents | When corticosteroids are administered concomitantly with potassium-depleting agents (i.e., amphotericin B, diuretics), observe patients closely for development of hypokalemia. There have been cases reported in which concomitant use of amphotericin B and hydrocortisone was followed by cardiac enlargement and congestive heart failure.
Antibiotics | Macrolide antibiotics have been reported to cause a significant decrease in corticosteroid clearance.
Anticholinesterases | Concomitant use of anticholinesterase agents and corticosteroids may produce severe weakness in patients with myasthenia gravis. If possible, withdraw anticholinesterase agents at least 24 hours before initiating corticosteroid therapy.
Anticoagulants, oral | Coadministration of corticosteroids and warfarin usually results in inhibition of response to warfarin, although there have been some conflicting reports. Therefore, monitor coagulation indices frequently to maintain the desired anticoagulant effect.
Antidiabetics | Because corticosteroids may increase blood glucose concentrations, dosage adjustments of antidiabetic agents may be required.
Antitubercular drugs | Serum concentrations of isoniazid may be decreased.
CYP 3A4 inducers (e.g., barbiturates, phenytoin, carbamazepine, and rifampin) | Drugs which induce hepatic microsomal drug metabolizing enzyme activity may enhance metabolism of corticosteroids and require that the dosage of corticosteroid be increased.
CYP 3A4 inhibitors (e.g., ketoconazole) | Ketoconazole, a strong CYP3A4 inhibitor, has been reported to decrease the metabolism of certain corticosteroids by up to 60% leading to an increased risk of corticosteroid side effects.
Cholestyramine | Cholestyramine may increase the clearance of corticosteroids.
Cyclosporine | Increased activity of both cyclosporine and corticosteroids may occur when the two are used concurrently. Convulsions have been reported with this concurrent use.
Digitalis glycosides | Patients on digitalis glycosides may be at increased risk of arrhythmias due to hypokalemia.
Estrogens, including oral contraceptives | Estrogens may decrease the hepatic metabolism of certain corticosteroids, thereby increasing their effect.
Nonsteroidal anti-inflammatory drugs (NSAIDs) | Concomitant use of aspirin (or other nonsteroidal anti-inflammatory drugs) and corticosteroids increases the risk of gastrointestinal side effects. Aspirin should be used cautiously in conjunction with corticosteroids in hypoprothrombinemia. The clearance of salicylates may be increased with concurrent use of corticosteroids.
Skin tests | Corticosteroids may suppress reactions to allergy related skin tests.
Vaccines | Patients on prolonged corticosteroid therapy may exhibit a diminished response to toxoids and live or inactivated vaccines due to inhibition of antibody response. Corticosteroids may also potentiate the replication of some organisms contained in live attenuated vaccines. If possible, defer routine administration of vaccines or toxoids until corticosteroid therapy is discontinued.

8 USE IN SPECIFIC POPULATIONS

8.1 Pregnancy

Risk Summary

There are no data regarding the use of ZILRETTA in pregnant women to inform a drug associated risk of adverse developmental outcomes. Published studies on the association between corticosteroids and fetal outcomes have reported inconsistent findings and have important methodological limitations. The majority of published literature with corticosteroid exposure during pregnancy includes the oral, topical and inhaled dosage formulations; therefore, the applicability of these findings to a single intra-articular injection of triamcinolone acetonide is limited. In animal reproductive studies from the published literature, pregnant mice, rats, rabbits, or primates administered triamcinolone acetonide during the period of organogenesis at doses that produced exposures less than the maximum recommended human dose (MRHD) caused resorptions, decreased fetal body weight, craniofacial and/or other abnormalities such as omphalocele (see Data).

The estimated background risk of major birth defects and miscarriage for the indicated population is unknown. All pregnancies have a background risk of birth defect, loss, or other adverse outcomes. In the U.S. general population, the estimated risk of major birth defects and miscarriage in clinically recognized pregnancies is 2% to 4% and 15% to 20%, respectively.

Data

Animal Data

The exposure margins listed below are based on body surface area comparisons (mg/m^2) to the highest daily triamcinolone acetonide exposure at the MRHD of 32 mg triamcinolone acetonide via ZILRETTA.

Pregnant mice dosed with triamcinolone acetonide via intramuscular or subcutaneous injection at doses equivalent to 0.8 times the MRHD or higher during organogenesis caused cleft palate and a higher rate of resorption. In pregnant rats dosed with triamcinolone acetonide via intramuscular or subcutaneous injection at doses equivalent to 0.3 times the MRHD or higher during organogenesis caused developmental abnormality (cleft palate, omphalocele, late resorption, and growth retardation) and fetal mortality. No notable maternal toxicity was observed in rodents.

Pregnant rabbits dosed with triamcinolone acetonide via intramuscular injection for 4 days during organogenesis at doses equivalent to 0.15 times the MRHD or higher caused resorption and cleft palate. No notable maternal toxicity was observed.

Pregnant primates dosed with triamcinolone acetonide via intramuscular injection for 4 days during organogenesis at doses equivalent to 3 times the MRHD or higher caused severe craniofacial CNS and skeletal/visceral malformation and higher prenatal death. No notable maternal toxicity was observed.

No peri- and post-natal development studies of triamcinolone acetonide in animals have been conducted.

8.2 Lactation

Risk Summary

There are no available data on the presence of triamcinolone acetonide in either human or animal milk, the effects on the breastfed infant, or the effects on milk production. However, corticosteroids have been detected in human milk and may suppress milk production. It is not known whether intra-articular administration of ZILRETTA could result in sufficient systemic absorption to produce detectable quantities in human milk. The developmental and health benefits of breastfeeding should be considered along with the mother's clinical need for ZILRETTA and any potential adverse effects on the breastfed infant from ZILRETTA or from the underlying maternal condition.

8.3 Females and Males of Reproductive Potential

Corticosteroids may result in menstrual pattern irregularities such as deviations in timing and duration of menses and an increased or decreased loss of blood.

8.4 Pediatric Use

The safety and effectiveness of ZILRETTA in pediatric patients have not been established.

The adverse effects of corticosteroids in pediatric patients are similar to those in adults. Carefully observe pediatric patients, including weight, height, linear growth, blood pressure, intraocular pressure, and clinical evaluation for the presence of infection, psychosocial disturbances, thromboembolism, peptic ulcers, cataracts, and osteoporosis. Weigh potential growth effects of treatment against clinical benefits obtained and the availability of treatment alternatives.

8.5 Geriatric Use

Of the total number of patients administered 32 mg ZILRETTA in clinical studies (N=424), 143 patients were 65 years of age or older. No overall differences in safety or effectiveness were observed between elderly and younger subjects, and other reported clinical experience with triamcinolone acetonide has not identified differences in responses between the elderly and younger patients, but greater sensitivity of some older individuals cannot be ruled out.

11 DESCRIPTION

ZILRETTA (triamcinolone acetonide extended-release injectable suspension) is a microsphere formulation of triamcinolone acetonide, a corticosteroid, to be administered by intra-articular injection.

ZILRETTA is formulated in 75:25 poly(lactic-co-glycolic acid) (PLGA) microspheres with a nominal drug load of 25% (w/w) and is provided as a sterile white to off-white powder. ZILRETTA is prepared with a supplied diluent containing an isotonic, sterile, aqueous solution of sodium chloride (NaCl; 0.9% w/w), sodium carboxymethylcellulose (CMC; 0.5% w/w), polysorbate-80 (0.1% w/w) and with sodium hydroxide (NaOH) and hydrochloric acid (HCl) as pH adjusters, as required to form a 5 mL sterile suspension intended for intra-articular injection.

Active Ingredient

The chemical name for triamcinolone acetonide is 9-fluoro-11β,16α,17,21-tetrahydroxypregna-1,4-diene- 3,20-dione cyclic 16,17-acetal with acetone. Its structural formula is:

MW 434.50 with a molecular formula of C24H31FO6

Triamcinolone acetonide occurs as a white to almost white, crystalline powder having not more than a slight odor and is practically insoluble in water and very soluble in alcohol. Each vial of ZILRETTA powder contains 40 mg of triamcinolone acetonide in 160 mg of microspheres, resulting in 32 mg of deliverable triamcinolone acetonide when prepared according to the Instructions for Use.

12 CLINICAL PHARMACOLOGY

12.1 Mechanism of Action

Triamcinolone acetonide is a corticosteroid with anti-inflammatory and immunomodulating properties. It binds to and activates the glucocorticoid receptor, leading to activation of anti-inflammatory transcription factors such as lipocortins and inhibition of inflammatory transduction pathways by blocking the release of arachidonic acid and preventing the synthesis of prostaglandins and leukotrienes.

12.2 Pharmacodynamics

Studies indicate that following a single intramuscular dose of 60 to 100 mg of immediate-release triamcinolone acetonide injectable suspension, adrenal suppression occurs within 24 to 48 hours and then gradually returns to normal, usually in 30 to 40 days. To assess potential effects of the systemic levels of triamcinolone acetonide associated with a single intra-articular (IA) administration of ZILRETTA on hypothalamic pituitary adrenal (HPA) axis function, serum and urine cortisol levels were monitored over 6 weeks post injection. Adrenal suppression with ZILRETTA occurred within 12-24 hours and then gradually returned to normal, within 30-42 days.

Corticosteroids may increase blood glucose concentrations.

In a study where 18 patients with osteoarthritis knee pain and controlled type 2 diabetes mellitus received a single IA injection of ZILRETTA into the knee, the change from baseline in average blood glucose over the 72 hours after injection as measured by a continuous glucose monitoring device was 8.2 mg/dL (95% confidence interval 0.1, 29.2).

12.3 Pharmacokinetics

ZILRETTA is an extended-release dosage form consisting of microspheres of poly(lactic-co-glycolic acid) (PLGA) containing triamcinolone acetonide. Plasma pharmacokinetic parameters for triamcinolone acetonide following IA administration of ZILRETTA or 40 mg immediate-release triamcinolone acetonide into the knee are provided in Table 4.

Table 4: Summary of Mean (SD) Plasma Pharmacokinetic Parameters for Triamcinolone Acetonide Following IA Administration of ZILRETTA or 40 mg Immediate-Release Triamcinolone Acetonide
Triamcinolone Acetonide PK Parameters [Median (min, max) values for tmax] | ZILRETTA (N=60) | Triamcinolone Acetonide (N=18)
Cmax (pg/mL) | 1,143.7 (611.06) | 21,062.2 (18,466.79)
AUC0-24 hour (pg∙h/mL) | 21,219.2 (11,325.62) | 297,545.3 (222,402.77)
AUC0-inf (pg∙h/mL) | 842,149.2 (1,062,004.97) [33 patients contributed to the analyses of these parameters] | 1,567,565.0 (1,246,330.95) [14 patients contributed to the analyses of these parameters]
tmax (h) | 7 (1, 1,008) | 6 (2, 24)
t1/2 (h) | 633.9 (893.0) | 146.9 (213.29)

13 NONCLINICAL TOXICOLOGY

13.1 Carcinogenesis, Mutagenesis, Impairment of Fertility

Carcinogenesis

Long-term animal studies to evaluate the carcinogenic potential of ZILRETTA have not been conducted.

Mutagenesis

Adequate mutagenicity studies have not been conducted with ZILRETTA.

Impairment of Fertility

Studies in animals to evaluate the impairment of fertility of ZILRETTA have not been conducted.

13.2 Animal Toxicology and/or Pharmacology

Single and repeat administrations (one injection every three months for a total of three injections) of ZILRETTA in non-arthritic knee joints of healthy dogs have been studied at ~1.9 times the maximum recommended human dose (MRHD) of 32 mg (based on estimated drug concentrations within the knee joints). ZILRETTA microspheres were degraded by approximately 4-and 6-months post dosing in single and repeat dose studies, respectively.

Single administration resulted in a slightly increased incidence, severity (minimal to slight), and/or duration of microscopic changes (infiltration of macrophages, lymphocytes, plasma cells and fibrosis) and decreased Safranin O staining (decreased proteoglycan content in the cartilage of the knees) compared to administration of an equivalent dose of immediate-release triamcinolone acetonide. These responses were mostly reversed after 6 to 9 months post injection.

Repeat administration resulted in an increase in the incidence, severity (minimal to slight) and duration of microscopic changes (infiltration of macrophages, lymphocytes, plasma cells, neutrophils; fibrosis; neovascularization; granulation tissue; and debris) and decreased Safranin O staining (decreased proteoglycan content in the cartilage of the knees) compared to the equivalent dose of immediate-release triamcinolone acetonide. These local responses were still reversing at 6 months post the last injection. No effect on the animals according to observations related to gait/walking, pain/discomfort in the injected knee, local swelling, local redness or local tenderness were noted.

The clinical relevance of these findings in the arthritic knee is unknown.

14 CLINICAL STUDIES

The efficacy of ZILRETTA was demonstrated in a multi-center, international, randomized, double-blind, parallel-arm, placebo- and active-controlled study in patients with osteoarthritis pain of the knee. A total of 484 patients (ZILRETTA 32 mg, N=161; placebo [saline], N=162; active control [a crystalline suspension, immediate-release formulation of triamcinolone acetonide 40 mg], N=161) were treated and followed for up to 24 weeks. Patients had a mean age of 62 (range 40 to 85 years); baseline demographics and disease characteristics were balanced across treatment arms. Twenty-five percent (25%) of patients had received at least one prior corticosteroid intra-articular injection more than 3 months prior to treatment. A total of 470 patients (97%) completed follow-up to Week 12, the time point for primary efficacy determination, and 443 (91.5%) completed to Week 24.

The primary efficacy endpoint comparing ZILRETTA to placebo was change from baseline at Week 12 in the weekly mean of the Average Daily Pain intensity scores (ADP) as assessed by a 0-10 Numeric Rating Scale (NRS). ZILRETTA demonstrated a statistically significant reduction in pain intensity at the primary endpoint vs placebo. ZILRETTA also demonstrated a reduction in pain intensity scores each week from Weeks 1 through 12 (Figure 1).

Figure 1: Weekly Change from Baseline to Week 12 in Average Daily Pain

16 HOW SUPPLIED/STORAGE AND HANDLING

Description | NDC | Presentation/How Supplied
ZILRETTA | NDC 65250-003-01 | ZILRETTA (triamcinolone acetonide extended-release injectable suspension) single-dose kit.
Kit Contents
ZILRETTA microsphere powder | NDC 65250-001-01 | Single-dose vial to deliver 32 mg of triamcinolone acetonide supplied as a sterile, white to off-white powder in a cerium glass (clear) vial with a rubber stopper and an aluminum seal with a gray plastic cap.
Diluent | NDC 65250-002-01 | 5 mL single-dose vial supplied as a sterile, colorless to pale yellow, clear liquid solution of 0.9% w/w sodium chloride (normal saline) containing 0.5% w/w sodium carboxymethylcellulose, and 0.1% w/w polysorbate-80 in a glass vial with a rubber stopper, aluminum seal and white plastic cap.
Sterile vial adapter

STORAGE

To maintain expiry period, refrigerate the ZILRETTA single-dose kit 2°-8°C (36°-46°F) before use.

If refrigeration is unavailable, store the ZILRETTA single-dose kit in the sealed, unopened kit at temperatures not exceeding 25°C (77°F) for up to three weeks and then discard. Do not expose the ZILRETTA single-dose kit to temperatures above 25°C (77°F).

Do not freeze. Store vials in carton.

17 PATIENT COUNSELING INFORMATION

Increased Risk of Infections

Inform patients that they may be more likely to develop infections when taking corticosteroids. Instruct patients to contact their health care provider if they develop fever or other signs or symptoms of infection.

Advise patients who have not been vaccinated to avoid exposure to chicken pox or measles. Instruct patients to contact their health care provider immediately if they are exposed [see Warnings and Precautions (5.5)].

Risk of Drug Interactions

There are a number of medicines that can interact with corticosteroids such as triamcinolone acetonide. Advise patients to alert their health care provider(s) to assess the need to adjust their medication(s) [see Drug Interactions (7)].

Risk of Adverse Psychiatric Reactions

Inform patients that corticosteroid use may be associated with adverse psychiatric reactions. Advise patients and/or caregivers to immediately report any new or worsening behavioral or mood disturbances to their health care provider [see Warnings and Precautions (5.12)].

Manufactured for Pacira Pharmaceuticals, Inc., a wholly owned subsidiary of Pacira BioSciences, Inc. San Diego, CA 92121 USA

Trademark of Pacira Therapeutics, Inc., a wholly owned subsidiary of Pacira BioSciences, Inc.

©2024 Pacira Pharmaceuticals, Inc. All rights reserved.

For more information, go to ZILRETTA.com or call 1-844-353-9466.

Part Number: 60-009-08
Version: 8, 11/2024

Instructions for Use

ZILRETTA®
(triamcinolone acetonide
extended-release injectable suspension)

For intra-articular injection only

Single-dose device
Do not reuse.

IMPORTANT INFORMATION

- ZILRETTA must be prepared using only the diluent supplied in the kit.
- To ensure proper dosing, it is important that you follow the preparation and administration steps outlined in these instructions.
- Promptly inject ZILRETTA after preparation to avoid settling of the suspension.
- ZILRETTA is supplied as a single-dose kit and administered as a suspension containing microspheres.
- The ZILRETTA powder vial contains an overfill to allow the appropriate dose to be withdrawn. ZILRETTA is a suspension product and it is normal for some residue to be left behind on the vial walls after withdrawing the contents.
- Parenteral drug products should be inspected visually for particulate matter and discoloration prior to administration.
- Use proper aseptic technique throughout the dose preparation and administration procedure.
- Inspect all kit components to confirm they have not expired and the seals are intact.
- For additional information, visit www.zilretta.com or call Pacira Pharmaceuticals, Inc. at 1-844-353-9466.

MATERIALS REQUIRED (Fig. 1)

Supplied

- One 32 mg vial of ZILRETTA microsphere powder
- One 5 mL vial of sterile diluent
- One sterile vial adapter

Not Supplied

- Three sterile needles, 21-gauge, 1½" length
- One sterile Luer Lock compatible syringe, 5 mL
- Sterile alcohol pads
- Paper towels or pad to cushion vial tapping (not shown in Fig. 1)
- Medical-grade gloves (not shown in Fig. 1)

Figure 1

1. Vial Preparation

Loosen Powder.

Place two paper towels or a pad on a properly-cleaned hard surface.

Grip the top of the ZILRETTA powder vial and tap firmly and repeatedly on the padded surface. Tap the vial until excess powder is dislodged from the vial and stopper (Fig. 2). Before continuing, ensure that powder moves freely within the vial.

Figure 2

Inspect ZILRETTA Powder Vial.

As shown in Figure 3, the vial on the left, with the X, requires additional tapping because the powder is not properly dislodged. The vial on the right shows the powder properly dislodged and ready for the next step.

Figure 3

Remove Caps.

Remove the flip-off caps from the ZILRETTA powder and diluent vials (Fig. 4).

Figure 4

Clean Vials.

Clean the ZILRETTA powder and diluent vial tops with an alcohol pad.

Use a separate alcohol pad for each vial.

Peel Off Vial Adapter Cover.

Peel off the paper cover from the vial adapter package (Fig. 5).

Leave the adapter in the plastic holder.

Figure 5

Attach Vial Adapter to ZILRETTA Powder Vial.

Grip the plastic holder that contains the vial adapter.

As shown in Figure 6, place the ZILRETTA powder vial on a flat surface. In a vertical orientation, gently push the adapter down onto the ZILRETTA powder vial until the spike on the adapter penetrates the rubber stopper on the ZILRETTA powder vial. The adapter will snap into place.

Figure 6

2. Diluent Preparation

Attach Needle.

Attach a needle to the syringe and remove the needle guard.

Withdraw Diluent.

With a syringe and needle, withdraw 5 mL of diluent.

Replace the needle guard.

3. Dose Preparation

Remove Holder.

Remove the plastic holder from the vial adapter (Fig. 7).

Figure 7

Remove Needle.

Remove the needle from the syringe containing diluent.

Attach Diluent Syringe.

Attach the syringe onto the vial adapter by pushing down and turning clockwise until you feel resistance (Fig. 8).

Figure 8

Transfer Diluent.

Slowly and completely push down the syringe plunger to transfer the diluent into the ZILRETTA powder vial (Fig. 9).

Note: Equalize the pressure in the syringe by slowly pulling back the plunger to the 5 mL mark. Ensure that no solution is drawn back into the syringe at this stage.

Figure 9

Mix Diluent and Powder (Fig.10).

With the syringe still attached to the ZILRETTA powder vial, hold the syringe and vial at a slight angle. Tap the bottom edge of the vial firmly and repeatedly, in a circular motion, on the padded surface.

Swirl gently every five or six taps. Tap for at least one minute until all powder is completely dispersed.

Note: Avoid vigorous shaking of the vial to minimize foaming.

Note: At least one minute of tapping and gentle swirling is required to achieve uniform suspension.

Figure 10

Inspect Vial.

Inspect the ZILRETTA powder vial to ensure no clumped powder is visible and a uniform suspension has been achieved. A properly mixed suspension will be milky white, contain no clumps, and move freely down the vial wall.

As shown in Figure 11, the vial on the left, with the X, requires more tapping and gentle swirling because the powder is not mixed properly with the diluent. The vial on the right shows the powder properly mixed and ready for the next step.

Figure 11

Note: If needed, the ZILRETTA suspension can be stored in the vial for up to 4 hours at ambient conditions. The syringe must remain on the vial adapter while the suspension remains in the vial.

Withdraw Contents into Syringe.

Swirl the vial gently for at least 10 seconds to ensure the powder is fully suspended. Immediately depress the plunger fully and then invert the syringe so the vial is directly on top of the syringe (Fig. 12).

Hold the syringe in a completely vertical position, per the illustration on the right, in Figure 12.

Withdraw the full contents from the ZILRETTA vial into the syringe.

Figure 12

Note: ZILRETTA is a suspension product and it is normal for some residue to be left behind on the vial walls after withdrawing the contents.

Remove Syringe.

Remove the syringe from the vial adapter by turning counter-clockwise.

Remove Air Bubbles.

Attach a new needle to the syringe and remove the needle guard.

Inspect for bubbles with the syringe held in a completely vertical position (needle upward). If bubbles are observed, gently tap the syringe with your finger until the bubbles rise to the top. Eliminate all bubbles by slowly depressing the plunger to displace the air from the syringe.

Replace the needle guard.

Attach New Needle.

Remove and discard the needle.

Attach a new needle.

4. Administration

Invert Syringe.

To ensure the powder is suspended, gently invert the syringe containing ZILRETTA several times just prior to administration, as shown in Figure 13.

Grip the syringe firmly and turn it so the syringe plunger is pointing straight down. Then turn the syringe gently, 180 degrees, until the plunger is pointing straight up.

Invert the syringe several times to ensure a properly mixed suspension.

Figure 13

A properly mixed suspension will be uniformly milky white and contain no clumps.

Inspect Syringe.

As shown in Figure 14, the syringe on the left, with the X, requires more inversions (turning) to properly mix the suspension. The syringe on the right shows the suspension properly mixed and ready for the next step.

Figure 14

Administer ZILRETTA.

The usual technique for intra-articular injection should be followed.

Aspiration of synovial fluid may be performed based on clinical judgment prior to administration of ZILRETTA.

Do not reuse excess ZILRETTA. Any excess suspension in the vial should be thrown away immediately after the injection. Leftover ZILRETTA in the vial must never be reused for another injection.

Note: The entire contents of the syringe must be injected to ensure the intended dose of ZILRETTA is delivered.

Note: Discard all used components in an appropriate medical waste container according to local regulations.

Note: ZILRETTA is for intra-articular use only. ZILRETTA is not intended for epidural, intrathecal, intravenous, intraocular, intramuscular, intradermal, or subcutaneous use.

Part Number: 60-005-03
Rev: 03/2022

PRINCIPAL DISPLAY PANEL - Kit Carton

NDC 65250-003-01
Rx Only

Zilretta®
(triamcinolone acetonide extended-release
injectable suspension)

32 mg per vial

For intra-articular injection only.
Single-dose kit. Discard unused portion.

Must be reconstituted
with the supplied diluent.

This carton contains:

- 1 vial of Zilretta
  microsphere powder
- 1 vial of diluent (5mL)
  for Zilretta
- 1 sterile vial adapter

PACIRA
PHARMACEUTICALS, INC.

PRINCIPAL DISPLAY PANEL - 32 mg Vial Label

NDC 65250-001-01
Rx Only

Zilretta®
(triamcinolone acetonide extended-release
injectable suspension)

32 mg per vial

For intra-articular injection only.

Must be reconstituted
with the supplied diluent.

PACIRA
PHARMACEUTICALS, INC.

PRINCIPAL DISPLAY PANEL - 5 mL Vial Label

NDC 65250-002-01
Rx Only

DILUENT
for use with Zilretta®

5 mL
Sterile single-use vial

Do not administer directly.

PACIRA
PHARMACEUTICALS, INC.